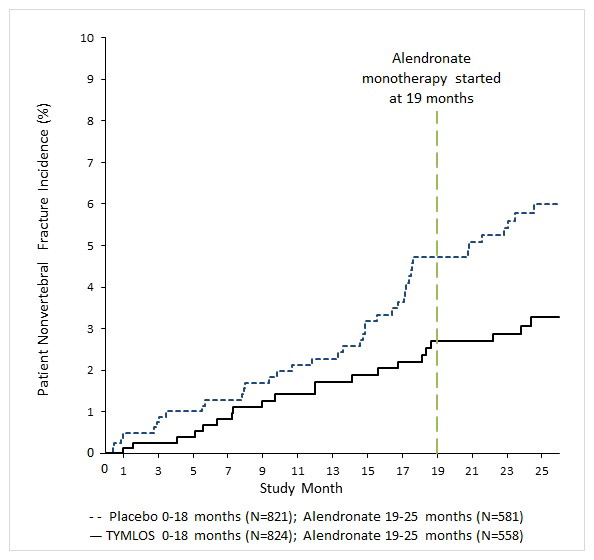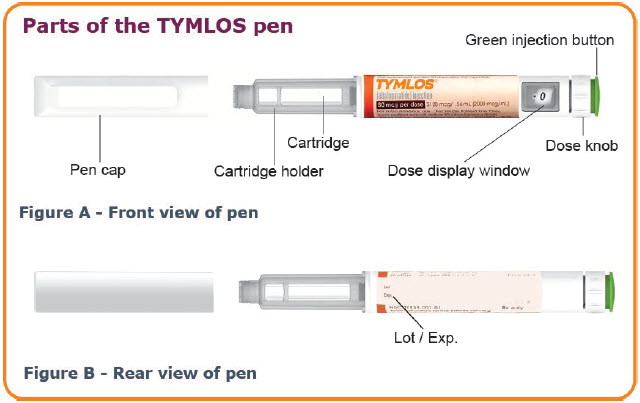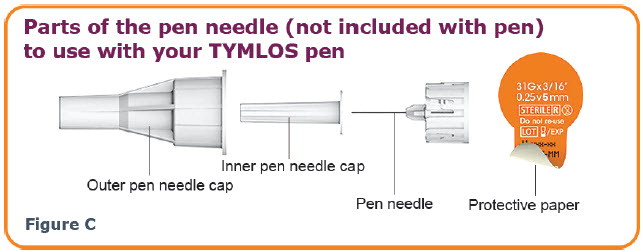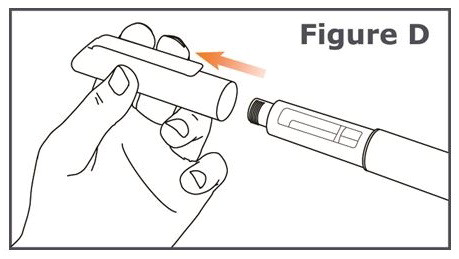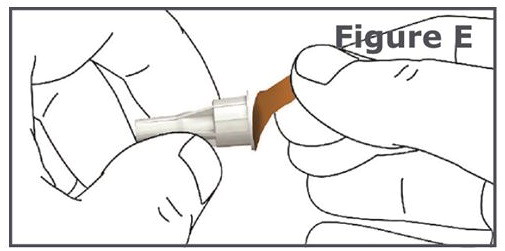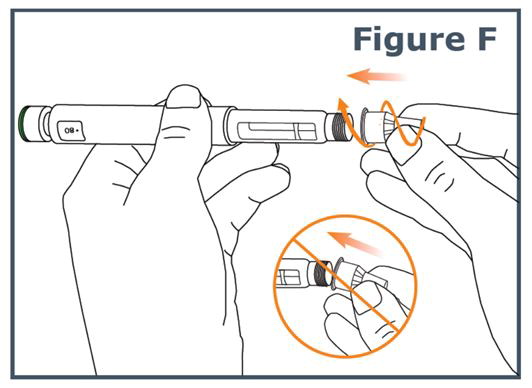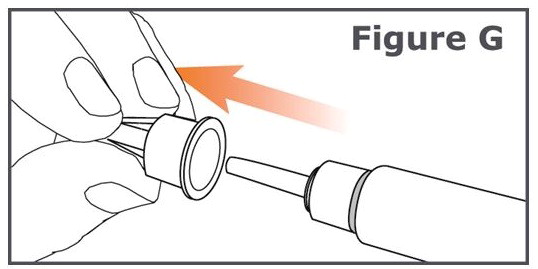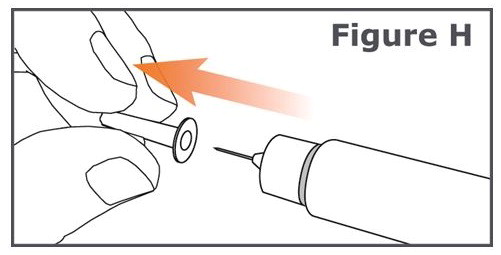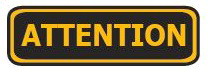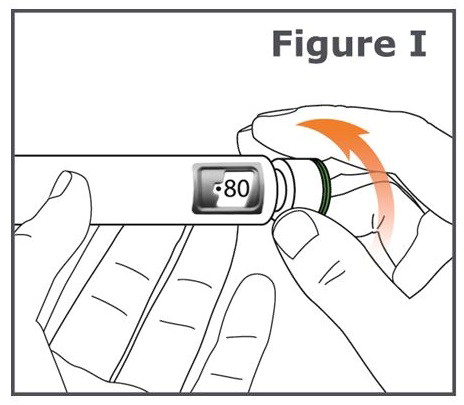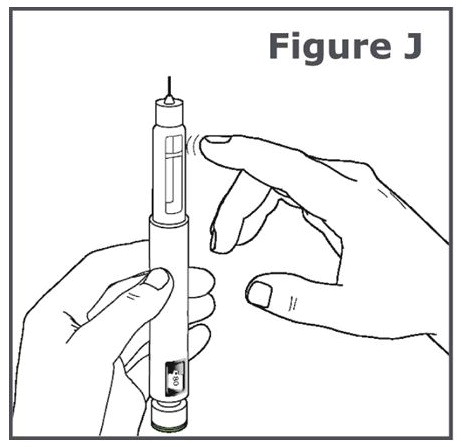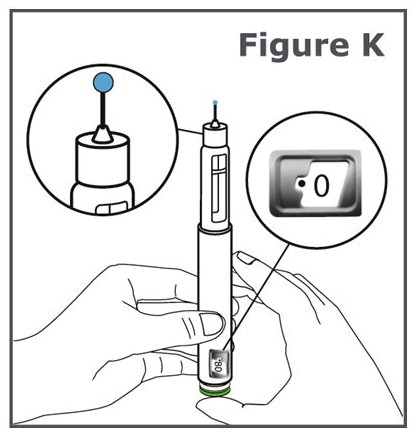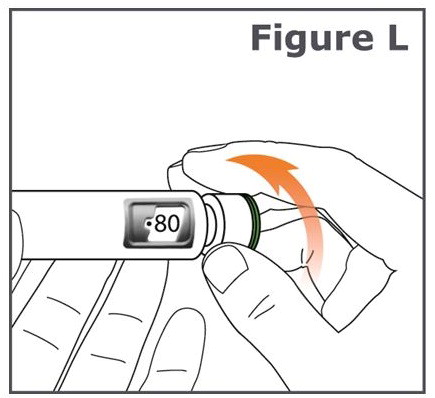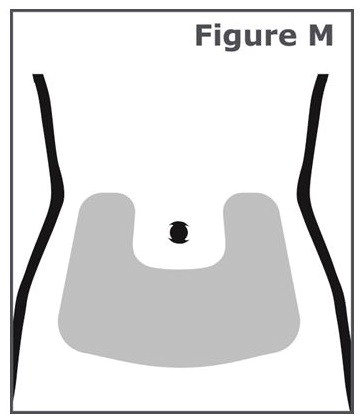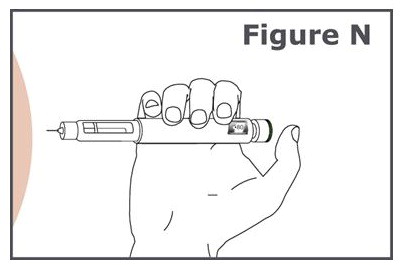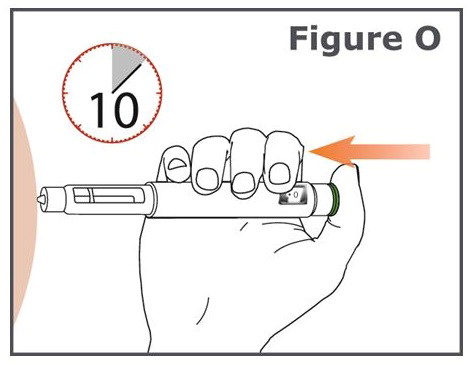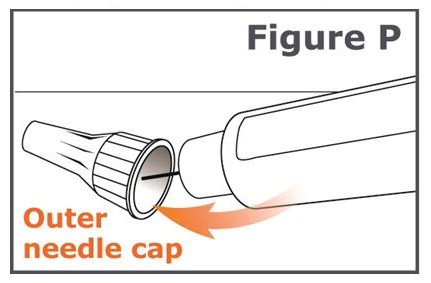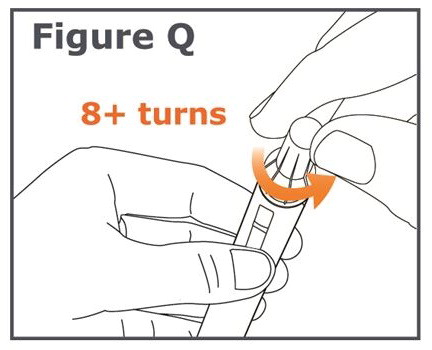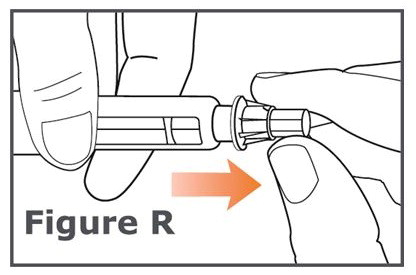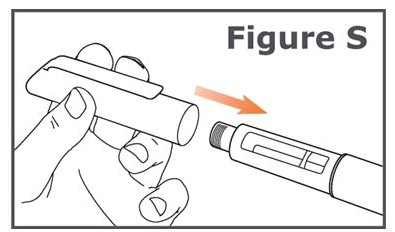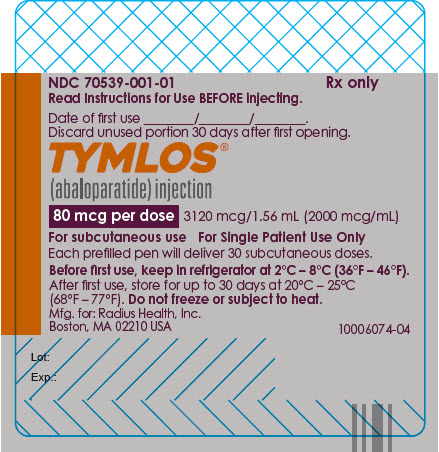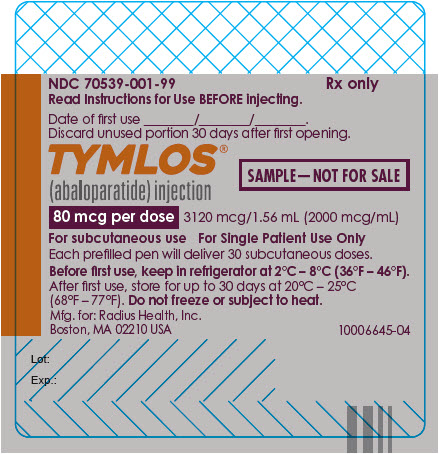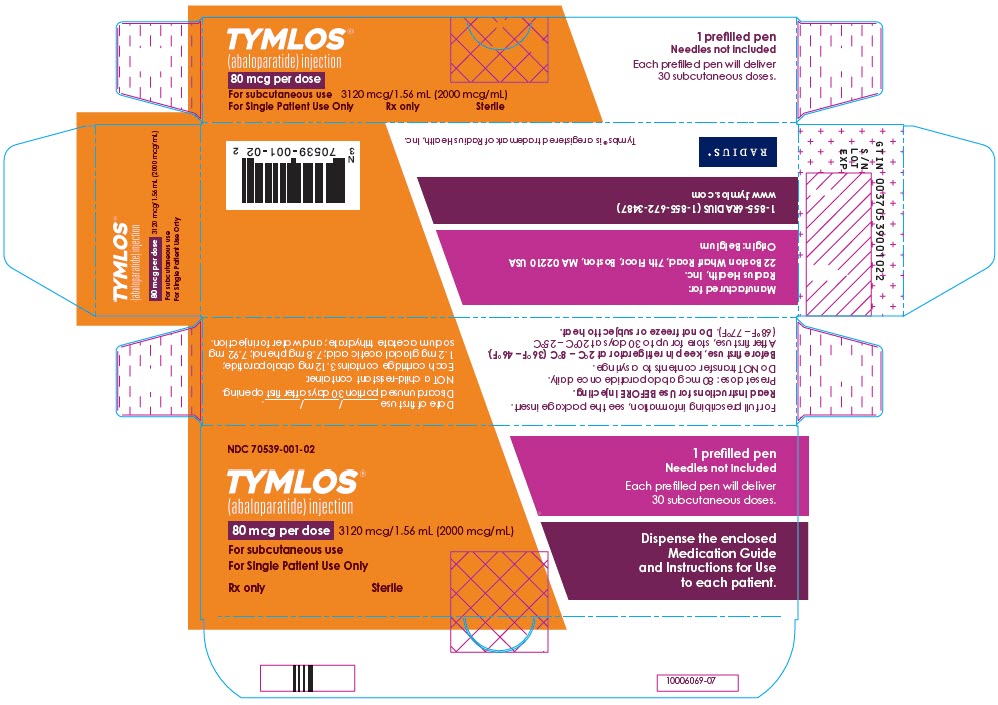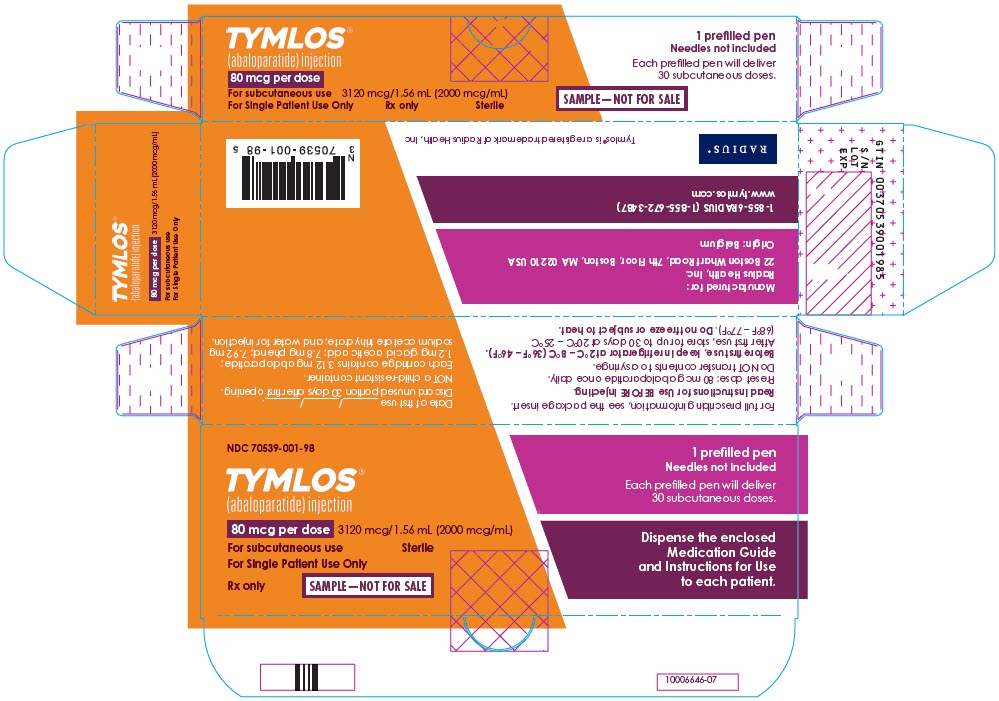 DRUG LABEL: Tymlos
NDC: 70539-001 | Form: INJECTION, SOLUTION
Manufacturer: Radius Health, Inc.
Category: prescription | Type: HUMAN PRESCRIPTION DRUG LABEL
Date: 20250404

ACTIVE INGREDIENTS: ABALOPARATIDE 3.12 mg/1.56 mL
INACTIVE INGREDIENTS: PHENOL 7.8 mg/1.56 mL; SODIUM ACETATE 7.92 mg/1.56 mL; ACETIC ACID 1.2 mg/1.56 mL; WATER

HIGHLIGHTS OF PRESCRIBING INFORMATION

These highlights do not include all the information needed to use TYMLOS safely and effectively. See full prescribing information for TYMLOS.
TYMLOS® (abaloparatide) injection, for subcutaneous use
Initial U.S. Approval: 2017

1 INDICATIONS AND USAGE

TYMLOS is a human parathyroid hormone related peptide [PTHrP(1-34)] analog indicated for the:

- Treatment of postmenopausal women with osteoporosis at high risk for fracture or patients who have failed or are intolerant to other available osteoporosis therapy. (1.1)
- Treatment to increase bone density in men with osteoporosis at high risk for fracture or patients who have failed or are intolerant to other available osteoporosis therapy. (1.2)

2 DOSAGE AND ADMINISTRATION

- Recommended dosage is 80 mcg subcutaneously once daily; patients should receive supplemental calcium and vitamin D if dietary intake is inadequate. (2.1)
- Administer as a subcutaneous injection into periumbilical region of abdomen. (2.2)
- Administer initially where the patient can sit or lie down in case symptoms of orthostatic hypotension occur. (2.2, 5.2)

3 DOSAGE FORMS AND STRENGTHS

Injection: 3120 mcg/1.56 ml (2000 mcg/ml) of abaloparatide in clear, colorless solution in a single-patient-use prefilled pen. The prefilled pen delivers 30 daily doses of 80 mcg abaloparatide in 40 mcl. (3)

4 CONTRAINDICATIONS

Known hypersensitivity to TYMLOS. (4)

5 WARNINGS AND PRECAUTIONS

- Osteosarcoma: Avoid use in patients with increased risk of osteosarcoma including patients with open epiphyses, metabolic bone diseases including Paget's disease, bone metastases or history of skeletal malignancies, prior external beam or implant radiation therapy involving the skeleton, and hereditary disorders predisposing to osteosarcoma. (5.1)
- Orthostatic Hypotension: Instruct patients to sit or lie down if symptoms develop after dose administration. (5.2)
- Hypercalcemia: Avoid use in patients with pre-existing hypercalcemia and those known to have an underlying hypercalcemic disorder, such as primary hyperparathyroidism. (5.3)
- Hypercalciuria and Urolithiasis: Monitor urine calcium if pre-existing hypercalciuria or active urolithiasis are suspected. (5.4)

6 ADVERSE REACTIONS

- Osteoporosis in postmenopausal women: The most common adverse reactions (incidence ≥2%) are hypercalciuria, dizziness, nausea, headache, palpitations, fatigue, upper abdominal pain, and vertigo. (6.1)
- Osteoporosis in men: The most common adverse reactions (incidence ≥2%) are injection site erythema, dizziness, arthralgia, injection site swelling, injection site pain, contusion, nausea, diarrhea, abdominal distension, abdominal pain, and bone pain. (6.1)

To report SUSPECTED ADVERSE REACTIONS, contact Radius Health, Inc. at 1-855-672-3487 or FDA at 1-800-FDA-1088 or www.fda.gov/medwatch.

FULL PRESCRIBING INFORMATION

1 INDICATIONS AND USAGE

1.1 Treatment of Postmenopausal Women with Osteoporosis at High Risk for Fracture

TYMLOS is indicated for the treatment of postmenopausal women with osteoporosis at high risk for fracture (defined as a history of osteoporotic fracture or multiple risk factors for fracture), or patients who have failed or are intolerant to other available osteoporosis therapy. In postmenopausal women with osteoporosis, TYMLOS reduces the risk of vertebral fractures and nonvertebral fractures.

1.2 Treatment to Increase Bone Density in Men with Osteoporosis at High Risk for Fracture

TYMLOS is indicated to increase bone density in men with osteoporosis at high risk for fracture (defined as a history of osteoporotic fracture or multiple risk factors for fracture), or patients who have failed or are intolerant to other available osteoporosis therapy.

2 DOSAGE AND ADMINISTRATION

2.1 Recommended Dosage

- The recommended dosage of TYMLOS is 80 mcg administered subcutaneously once daily.
- Patients should receive supplemental calcium and vitamin D if dietary intake is inadequate.

2.2 Administration Instructions

- Administer TYMLOS as a subcutaneous injection into the periumbilical region of the abdomen. Rotate the site of the injection every day and administer at approximately the same time every day. Do not administer intravenously or intramuscularly.
- Administer the first several doses where the patient can sit or lie down if necessary, in case symptoms of orthostatic hypotension occur [see Warnings and Precautions (5.2) and Adverse Reactions (6.1)].
- Visually inspect TYMLOS for particulate matter and discoloration prior to administration. TYMLOS is a clear and colorless solution. Do not use if solid particles appear or if the solution is cloudy or colored.
- Provide appropriate training and instruction to patients and caregivers on the proper use of the TYMLOS pen.

2.3 Treatment Duration

The safety and efficacy of TYMLOS have not been evaluated beyond 2 years of treatment. Use of the drug for more than 2 years during a patient's lifetime is not recommended.

3 DOSAGE FORMS AND STRENGTHS

Injection: 3120 mcg/1.56 mL (2000 mcg/mL) of abaloparatide in clear, colorless solution in a single-patient-use prefilled pen. The prefilled pen delivers 30 doses of TYMLOS, each containing 80 mcg of abaloparatide in 40 mcL.

4 CONTRAINDICATIONS

TYMLOS is contraindicated in patients with a history of systemic hypersensitivity to abaloparatide or to any component of the product formulation. Reactions have included anaphylaxis, dyspnea, and urticaria [see Adverse Reactions (6.2)].

5 WARNINGS AND PRECAUTIONS

5.1 Risk of Osteosarcoma

Abaloparatide caused a dose-dependent increase in the incidence of osteosarcoma in male and female rats after subcutaneous administration at exposures 4 to 28 times the human exposure at the clinical dose of 80 mcg [see Nonclinical Toxicology (13.1)]. It is unknown whether TYMLOS will cause osteosarcoma in humans.

Osteosarcoma has been reported in patients treated with a PTH-analog in the post marketing setting; however, an increased risk of osteosarcoma has not been observed in observational studies in humans. There are limited data assessing the risk of osteosarcoma beyond 2 years of TYMLOS and/or use of a PTH-analog [see Dosage and Administration (2.3) and Nonclinical Toxicology (13.1)].

Avoid TYMLOS use in patients with (these patients are at increased baseline risk of osteosarcoma):

- Open epiphyses (pediatric and young adult patients) (TYMLOS is not approved in pediatric patients) [see Use in Specific Populations (8.4)].
- Metabolic bone diseases other than osteoporosis, including Paget's disease of the bone.
- Bone metastases or a history of skeletal malignancies.
- Prior external beam or implant radiation therapy involving the skeleton.
- Hereditary disorders predisposing to osteosarcoma.

5.2 Orthostatic Hypotension

Orthostatic hypotension may occur with TYMLOS, typically within 4 hours of injection. Associated symptoms may include dizziness, palpitations, tachycardia, or nausea, and may resolve by having the patient lie down. For the first several doses, TYMLOS should be administered where the patient can sit or lie down if necessary [see Adverse Reactions (6.1)].

5.3 Hypercalcemia

TYMLOS may cause hypercalcemia. TYMLOS is not recommended in patients with pre-existing hypercalcemia or in patients who have an underlying hypercalcemic disorder, such as primary hyperparathyroidism, because of the possibility of exacerbating hypercalcemia [see Adverse Reactions (6.1)].

5.4 Hypercalciuria and Urolithiasis

TYMLOS may cause hypercalciuria. It is unknown whether TYMLOS may exacerbate urolithiasis in patients with active or a history of urolithiasis. If active urolithiasis or pre-existing hypercalciuria is suspected, measurement of urinary calcium excretion should be considered [see Adverse Reactions (6.1)].

6 ADVERSE REACTIONS

The following adverse reactions are described in greater detail in other sections:

- Orthostatic Hypotension [see Warnings and Precautions (5.2)]
- Hypercalcemia [see Warnings and Precautions (5.3)]
- Hypercalciuria and Urolithiasis [see Warnings and Precautions (5.4)]

6.1 Clinical Trials Experience

Because clinical studies are conducted under widely varying conditions, adverse reaction rates observed in the clinical studies of a drug cannot be directly compared to rates in the clinical studies of another drug and may not reflect the rates observed in practice.

Adverse Reactions from Clinical Trial in Postmenopausal Women with Osteoporosis

The safety of TYMLOS was evaluated in a randomized, multicenter, double-blind, placebo-controlled clinical trial in postmenopausal women with osteoporosis aged 49 to 86 years (mean age 69 years) who were randomized to receive 80 mcg of TYMLOS (N = 824) or placebo (N = 821), given subcutaneously once daily for 18 months [see Clinical Studies (14.1)].

In this study, the incidence of all-cause mortality was 0.4% in the TYMLOS group and 0.6% in the placebo group. The incidence of serious adverse events was 10% in the TYMLOS group and 11% in the placebo group. The percentage of patients who discontinued study drug due to adverse events was 10% in the TYMLOS group and 6% in the placebo group. The most common adverse reactions leading to study drug discontinuation in the TYMLOS group were nausea (2%), dizziness (1%), headache (1%), and palpitations (1%).

Table 1 shows the most common adverse reactions in the trial. These adverse reactions were generally not present at baseline, occurred more commonly with TYMLOS than with placebo, and occurred in at least 2% of the patients treated with TYMLOS.

Table 1: Common Adverse Reactions Reported in Postmenopausal Women with Osteoporosis*
Preferred term | TYMLOS (N=822) (%) | Placebo (N=820) (%)
Hypercalciuria | 11 | 9
Dizziness | 10 | 6
Nausea | 8 | 3
Headache | 8 | 6
Palpitations | 5 | 0.4
Fatigue | 3 | 2
Abdominal pain upper | 3 | 2
Vertigo | 2 | 2
* Adverse reactions reported in ≥2% of TYMLOS-treated patients.

Orthostatic Hypotension

In the clinical trial of women with postmenopausal osteoporosis, the incidence of orthostatic blood pressure decline ≥20 mmHg systolic or ≥10 mmHg diastolic at 1 hour after the first injection was 4% in the TYMLOS group and 3% in the placebo group. At later time points the incidence was generally similar between the treatment groups. Adverse reactions of orthostatic hypotension were reported in 1% of patients receiving TYMLOS and 0.5% of patients receiving placebo. Dizziness was reported by more TYMLOS-treated patients (10%) compared to placebo (6%) [see Warnings and Precautions (5.2)].

Tachycardia

In women with postmenopausal osteoporosis, adverse reactions of tachycardia, including sinus tachycardia, were reported in 2% of patients receiving TYMLOS and 1% of patients in the placebo group. In 5 of the 13 patients receiving TYMLOS who experienced tachycardia, symptoms occurred within 1 hour of administration. TYMLOS has been associated with a dose-dependent increase in heart rate which developed within 15 minutes after injection and resolved in about 6 hours [see Clinical Pharmacology (12.2)].

Injection Site Reactions

During the first month of the trial, injection site reactions were assessed daily one-hour after injection. TYMLOS had a higher incidence than placebo of injection site redness (58% vs. 28%), edema (11% vs. 3%), and pain (10% vs. 7%). Severe redness, severe edema, and severe pain were reported among 2.9%, 0.4%, and 0.4% of the TYMLOS-treated patients.

Laboratory Abnormalities

Hypercalcemia

In the clinical trial of women with postmenopausal osteoporosis, TYMLOS caused increases in serum calcium concentrations [see Warnings and Precautions (5.3)]. The incidence of hypercalcemia, defined as albumin-corrected serum calcium ≥10.7 mg/dL at 4 hours following injection at any visit, was 3% in TYMLOS-treated patients and 0.1% with placebo. Pre-dose serum calcium was similar to baseline in both groups. There were 2 (0.2%) TYMLOS-treated patients and no placebo-treated patients who discontinued from the study due to hypercalcemia. The incidence of hypercalcemia with TYMLOS was higher in patients with mild or moderate renal impairment (4%) compared to patients with normal renal function (1%).

Increases in Serum Uric Acid

TYMLOS increased serum uric acid concentrations. In the postmenopausal osteoporosis trial, among patients with normal baseline uric acid concentrations, 25% of patients in the TYMLOS group and 6% of patients in the placebo group had at least one post-baseline concentration above the normal range. The hyperuricemia observed in TYMLOS-treated patients was not associated with an increase in adverse reactions of gout or arthralgia over that observed with placebo.

Hypercalciuria and Urolithiasis

In the clinical trial of women with postmenopausal osteoporosis, the overall incidence of urine calcium:creatinine ratio >400 mg/g was higher with TYMLOS than with placebo (20% vs 15%, respectively). Urolithiases were reported in 2.1% of TYMLOS-treated patients and 1.7% of placebo-treated patients.

Adverse Reactions from the Extension Study in Postmenopausal Women with Osteoporosis

Following 18 months of treatment with TYMLOS or placebo, 1139 women transitioned to treatment with alendronate 70 mg administered orally once weekly. The incidence of adverse events occurring during alendronate treatment was similar in patients with prior placebo or TYMLOS therapy [see Clinical Studies (14.1)].

Adverse Reactions from Clinical Trial in Men with Osteoporosis

The safety of TYMLOS was evaluated in a randomized, multicenter, double-blind, placebo-controlled clinical trial in men with osteoporosis aged 42 to 85 years (mean age 68 years) who were randomized to receive 80 mcg of TYMLOS (N = 149) or placebo (N = 79), given subcutaneously once daily for 12 months [see Clinical Studies (14.2)].

In this study, no patient from either treatment group had an adverse reaction with a fatal outcome during the trial. Serious adverse reactions were reported by 5.4% of subjects treated with TYMLOS and 5.1% of subjects in the placebo group. Adverse reactions leading to study drug discontinuation were reported for 6.7% of patients treated with TYMLOS and 5.1% of patients receiving placebo. The most common adverse reaction leading to study drug discontinuation in the TYMLOS group was dizziness (2%).

Table 2 shows the most common adverse reactions in the trial. These adverse reactions were generally not present at baseline, occurred more commonly with TYMLOS than with placebo and occurred in at least 2% of the patients treated with TYMLOS.

Table 2: Common Adverse Reactions Reported in Men with Osteoporosis [Adverse reactions reported in ≥2% of TYMLOS-treated patients.]
Preferred Term | TYMLOS (N=149) (%) | Placebo (N=79) (%)
Injection site erythema | 13 | 5
Dizziness | 9 | 1
Arthralgia | 7 | 1
Injection site swelling | 7 | 0
Injection site pain | 6 | 0
Contusion | 3 | 0
Abdominal distention | 3 | 0
Diarrhea | 3 | 0
Nausea | 3 | 0
Abdominal Pain | 2 | 0
Bone Pain | 2 | 0

Orthostatic Hypotension

In the clinical trial of men with osteoporosis, the incidence of orthostatic blood pressure declines of ≥20 mmHg systolic or ≥10 mmHg diastolic at 1 hour after the first injection was 6% in the TYMLOS group and 3% in the placebo group. Adverse reactions of orthostatic hypotension were reported in 1% of patients receiving TYMLOS and 0 patients receiving placebo. Dizziness was reported by more TYMLOS-treated patients (9%) compared to placebo (1%) [see Warnings and Precautions (5.2)].

Laboratory Abnormalities

Hypercalcemia

In the clinical trial of men with osteoporosis, TYMLOS caused increases in serum calcium concentrations [see Warnings and Precautions (5.3)]. The incidence of hypercalcemia, defined as albumin-corrected serum calcium ≥10.8 mg/dL at 4 hours following injection at any visit, was 3% in TYMLOS-treated patients and 0% with placebo. Pre-dose serum calcium was similar to baseline in both groups. The incidence of hypercalcemia, defined as albumin-corrected serum calcium ≥10.8 mg/dL at 4 hours following injection, with TYMLOS was higher in patients with mild or moderate renal impairment (4%) compared to patients with normal renal function (0%).

Increases in Serum Uric Acid

TYMLOS increased serum uric acid concentrations. In the male osteoporosis trial, among patients with normal baseline uric acid concentrations, 7% of patients in the TYMLOS group and 6% of patients in the placebo group had at least one post-baseline concentration above the normal range. The hyperuricemia observed in TYMLOS-treated patients was not associated with an increase in adverse reactions of gout or arthralgia over that observed with placebo.

Hypercalciuria and Urolithiasis

In the clinical trial of men with osteoporosis, the overall incidence of urine calcium: creatinine ratio >400 mg/g was not greater with TYMLOS than with placebo. Urolithiases were reported in 2% of TYMLOS-treated patients and 1% of placebo-treated patients.

6.2 Postmarketing Experience

The following adverse reactions have been identified during the post-approval use of TYMLOS. Because these reactions are reported voluntarily from a population of uncertain size, it is not always possible to reliably estimate their frequency or establish a causal relationship to drug exposure.

- Abdominal distension, abdominal pain, abdominal discomfort
- Constipation, diarrhea, vomiting, decreased appetite
- Asthenia, lethargy, malaise, feeling abnormal, hot flush
- Insomnia
- Hypersensitivity and anaphylactic reactions, dyspnea (in the context of allergic reactions)
- Pruritus, rash
- Generalized pain and pain in bone, joint, back, and extremity
- Blood pressure increased
- Muscle spasms of the leg and back
- Injection site reactions including bruising, hemorrhage, pruritus, and rash

7 DRUG INTERACTIONS

No specific drug-drug interaction studies have been performed [see Clinical Pharmacology (12.3)].

8 USE IN SPECIFIC POPULATIONS

8.1 Pregnancy

Risk Summary

TYMLOS is not indicated for use in females of reproductive potential. There are no human data with TYMLOS use in pregnant women to inform any drug associated risks. Animal reproduction studies with abaloparatide have not been conducted.

8.2 Lactation

Risk Summary

TYMLOS is not indicated for use in females of reproductive potential. There is no information on the presence of abaloparatide in human milk, the effects on the breastfed infant, or the effects on milk production.

8.4 Pediatric Use

Safety and effectiveness of TYMLOS have not been established in pediatric patients. TYMLOS is not recommended for use in pediatric patients with open epiphyses or hereditary disorders predisposing to osteosarcoma because of an increased baseline risk of osteosarcoma [see Warnings and Precautions (5.1)].

8.5 Geriatric Use

Of the total number of patients in the postmenopausal osteoporosis clinical studies of TYMLOS, 82% were age 65 years and over, and 19% were age 75 years and over. In the male osteoporosis study, 74% were age 65 years and over and 23% were age 75 years or over. No overall differences in safety or effectiveness were observed between these subjects and younger subjects, but greater sensitivity of some older individuals cannot be ruled out.

8.6 Renal Impairment

No dosage adjustment is required for patients with mild, moderate, or severe renal impairment. A study of a single dose of TYMLOS 80 mcg given subcutaneously was conducted in subjects with normal renal function or mild, moderate, or severe renal impairment. The maximal concentration (Cmax) and area under the concentration-time curve (AUC) of abaloparatide increased 1.4- and 2.1-fold, respectively, in subjects with severe renal impairment, compared to subjects with normal renal function. Patients with severe renal impairment may have increased abaloparatide exposure that may increase the risk of adverse reactions; therefore, monitor for adverse reactions [see Clinical Pharmacology (12.3)].

10 OVERDOSAGE

In a clinical study, accidental overdose was reported in a patient who received 400 mcg in one day (5 times the recommended clinical dose); dosing was temporarily interrupted. The patient experienced asthenia, headache, nausea, and vertigo. Serum calcium was not assessed on the day of the overdose, but on the following day the patient's serum calcium was within the normal range. The effects of overdose may include hypercalcemia, nausea, vomiting, dizziness, tachycardia, orthostatic hypotension, and headache.

Overdosage Management

There is no specific antidote for TYMLOS. Treatment of suspected overdose should include discontinuation of TYMLOS, monitoring of serum calcium and phosphorus, and implementation of appropriate supportive measures, such as hydration. Based on the molecular weight, plasma protein binding and volume of distribution, abaloparatide is not expected to be dialyzable.

11 DESCRIPTION

TYMLOS injection for subcutaneous administration contains abaloparatide, a synthetic 34 amino acid peptide. Abaloparatide is an analog of human parathyroid hormone related peptide, PTHrP(1-34). It has 41% homology to hPTH(1-34) (human parathyroid hormone 1-34) and 76% homology to hPTHrP(1-34) (human parathyroid hormone-related peptide 1-34).

Abaloparatide has a molecular formula of C174H300N56O49 and a molecular weight of 3961 daltons with the amino acid sequence shown below:

Ala-Val-Ser-Glu-His-Gln-Leu-Leu-His-Asp-Lys-Gly-Lys-Ser-Ile-Gln-Asp-Leu-Arg-Arg-Arg-Glu-Leu-Leu-Glu-Lys-Leu-Leu-Aib-Lys-Leu-His-Thr-Ala-NH2

TYMLOS injection is supplied as a sterile, colorless, clear solution in a glass cartridge which is pre-assembled into a disposable single-patient-use pen. The pen is intended to deliver 30 once daily abaloparatide doses of 80 mcg in 40 mcL. Each cartridge contains 1.56 mL of TYMLOS solution which contains 3.12 mg of abaloparatide, and the following inactive ingredients: 1.2 mg glacial acetic acid, 7.8 mg phenol, 7.92 mg sodium acetate trihydrate, and water for injection to a target pH range of 5.1 to 5.2.

12 CLINICAL PHARMACOLOGY

12.1 Mechanism of Action

Abaloparatide is a PTHrP(1-34) analog which acts as an agonist at the PTH1 receptor (PTH1R). This results in activation of the cAMP signaling pathway in target cells. Once-daily administration of abaloparatide stimulates new bone formation on trabecular and cortical bone surfaces by stimulation of osteoblastic activity. In rats and monkeys, abaloparatide had an anabolic effect on bone, demonstrated by increases in BMD and bone mineral content (BMC) that correlated with increases in bone strength at vertebral and/or nonvertebral sites [see Nonclinical Toxicology (13.2)].

12.2 Pharmacodynamics

Effects on Markers of Bone Turnover

A dose-finding study of abaloparatide administered once daily for 24 weeks in postmenopausal women with osteoporosis demonstrated a dose-response relationship for BMD and bone formation markers.

Daily administration of TYMLOS to postmenopausal women with osteoporosis for 18 months increased the bone formation marker serum procollagen type I N-propeptide (sPINP) and the bone resorption marker serum collagen type I cross-linked C-telopeptide (sCTX). The increase in geometric mean sPINP levels peaked at Month 1 at 93% above baseline in postmenopausal women then decreased slowly over time to 45% above baseline at Month 18. The increase in geometric mean sCTX levels in postmenopausal women peaked at Month 3 at 26% above baseline then decreased to baseline levels by Month 18.

Daily administration of TYMLOS to men with osteoporosis for 12 months increased the bone formation marker sPINP and the bone resorption marker sCTX. The increase in geometric mean sPINP levels peaked at Month 1 at 133% above baseline in men then decreased slowly over time to 84% above baseline at Month 12. The increase in geometric mean sCTX levels in men peaked at Month 6 at 46% above baseline and was 35% above baseline by Month 12.

Cardiac Electrophysiology

A 4-way cross-over thorough QT/QTc study was conducted in 55 healthy subjects who received single doses of placebo, subcutaneous doses of abaloparatide at 80 mcg and 240 mcg (three times the recommended dose), and moxifloxacin 400 mg orally. Abaloparatide increased heart rate, with a mean peak increase of 15 beats per minute (bpm) and 20 bpm at the first time point (15 minutes) after dosing with 80 mcg and 240 mcg, respectively. There were no clinically meaningful effects of abaloparatide on QTcI (individually corrected QT intervals) or cardiac electrophysiology.

12.3 Pharmacokinetics

Following seven days of subcutaneous administration of abaloparatide 80 mcg, the mean (SD) abaloparatide exposure was 812 (118) pg/mL for Cmax and 1622 (641) pg∙hr/mL for AUC0–24 in postmenopausal women with osteoporosis.

Absorption

The median (range) time to peak concentration of abaloparatide 80 mcg was 0.51 hr (0.25 to 0.52 hr) following subcutaneous administration. The absolute bioavailability of abaloparatide in healthy women after subcutaneous administration of an 80 mcg dose was 36%.

Distribution

The in vitro plasma protein binding of abaloparatide was approximately 70%. The volume of distribution was approximately 50 L.

Elimination

Excretion

The mean (SD) half-life of abaloparatide is approximately 1 h. The peptide fragments are primarily eliminated through renal excretion.

Metabolism

No specific metabolism or excretion studies have been performed with TYMLOS. The metabolism of abaloparatide is consistent with non-specific proteolytic degradation into smaller peptide fragments, followed by elimination by renal clearance.

Specific Populations

Male and Female Subjects

Mean serum abaloparatide concentration-time profiles observed in a study conducted in healthy men with a mean (±SD) age of 53.1 (±6.9) years were comparable to those observed in the healthy women with a mean (±SD) age of 53.7 (±7.1) years using the same dosing regimen.

Geriatric Patients

No age-related differences in abaloparatide pharmacokinetics were observed in men and postmenopausal women ranging from 18 to 85 years of age.

Race

No differences in abaloparatide pharmacokinetics based on race were observed in clinical trials.

Patients with Renal Impairment

A single 80 mcg subcutaneous dose of abaloparatide was administered to male and female patients with renal impairment: 8 patients with mild renal impairment (CLCr 60 to 89 mL/min), 7 patients with moderate renal impairment (CLCr 30 to 59 mL/min), 8 patients with severe renal impairment (CLCr 15 to 29 mL/min), and 8 healthy subjects with normal renal function (CLCr 90 or greater mL/min) matched by sex, age, and body mass index (BMI). Abaloparatide Cmax increased 1.0-, 1.3-, and 1.4-fold in patients with mild, moderate, and severe renal impairment, compared to the healthy subjects with normal renal function. Abaloparatide AUC increased 1.2-, 1.7-, and 2.1-fold in patients with mild, moderate, and severe renal impairment, compared to the healthy subjects with normal renal function. Patients undergoing dialysis were not included in the study.

Drug Interactions

In vitro studies showed that abaloparatide, at therapeutic concentrations, does not inhibit or induce Cytochrome P450 enzymes. Abaloparatide is not a substrate of the renal transporters OAT1, OAT3, OCT2, MATE1, or MATE2K.

12.6 Immunogenicity

The observed incidence of anti-drug antibodies is highly dependent on the sensitivity and specificity of the assay. Differences in assay methods preclude meaningful comparisons of the incidence of anti-drug antibodies in the studies described below with the incidence of anti-drug antibodies in other studies, including those of abaloparatide or of other abaloparatide products.

Postmenopausal Women with Osteoporosis

Of the patients receiving TYMLOS for 18 months, 41% (318/773) developed anti-abaloparatide antibodies, and 26% (204/773) developed neutralizing antibodies to abaloparatide. Of the patients with anti-abaloparatide antibodies tested for cross-reactivity, 2.4% (7/297) developed cross-reactivity to PTHrP, of which 3 of the 7 patients developed neutralizing antibodies to PTHrP. Only 0.3% (1/297) developed cross-reactive antibodies to PTH, which were not neutralizing to PTH. Antibody formation did not appear to have any clinically significant impact on safety or efficacy endpoints, including bone mineral density (BMD) response, fracture reduction, or adverse events.

Most of the patients with anti-abaloparatide antibodies during treatment with TYMLOS, 86% (275/318), had follow-up antibody measurements every six months after completion of TYMLOS therapy until seroconverting to antibody negative or lost to follow-up. Among these patients, 127 remained antibody positive at 1 year after discontinuing treatment, 55 remained antibody positive at 2 years, and 6 remained antibody positive at 3 years.

Men with Osteoporosis

Of the male patients receiving TYMLOS for 12 months, 25% (36/142) developed anti-abaloparatide antibodies and 1.4% (2/142) developed neutralizing antibodies to abaloparatide. Of the patients with anti-abaloparatide antibodies tested for cross-reactivity, none developed cross-reactivity to PTHrP or PTH. Antibody formation did not appear to have any clinically significant impact on safety or efficacy endpoints, including bone mineral density (BMD) response or adverse events.

13 NONCLINICAL TOXICOLOGY

13.1 Carcinogenesis, Mutagenesis, Impairment of Fertility

Carcinogenesis

In a 2-year carcinogenicity study, abaloparatide was administered once daily to male and female Fischer rats by subcutaneous injection at doses of 10, 25, and 50 mcg/kg. These doses resulted in systemic exposures to abaloparatide that were 4, 16, and 28 times, respectively, the systemic exposure observed in humans following the recommended subcutaneous dose of 80 mcg (based on AUC comparisons). Neoplastic changes related to treatment with abaloparatide consisted of marked dose-dependent increases in osteosarcoma and osteoblastoma incidence in all male and female dose groups. The incidence of osteosarcoma was 0-2% in untreated controls and reached 87% and 62% in male and female high-dose groups, respectively. The bone neoplasms were accompanied by marked increases in bone mass.

The relevance of the rat findings to humans is uncertain. The use of TYMLOS is not recommended in patients at increased risk of osteosarcoma [see Warnings and Precautions (5.1)].

Mutagenesis

Abaloparatide was not genotoxic or mutagenic in a standard battery of tests including the Ames test for bacterial mutagenesis, the chromosome aberration test using human peripheral lymphocytes, and the mouse micronucleus test.

Impairment of Fertility

Abaloparatide effects on female fertility have not been assessed nonclinically. No adverse effects of abaloparatide on male fertility were observed in male rats. In a male rat fertility study, abaloparatide was administered via subcutaneous injection 2 weeks prior to mating, through the mating period and for approximately 2 weeks after the mating period (for total of 6 weeks) at doses of 10, 25 and 70 µg/kg/day. Abaloparatide did not cause adverse effect on mating, fertility indices, conception rate, reproductive organ weights or sperm parameters up to 70 µg/kg/day (28-fold the systemic exposure observed in humans following the recommended subcutaneous dose of 80 mcg (based on AUC comparisons).

13.2 Animal Toxicology and Pharmacology

In toxicity studies in rats and monkeys of up to 26-week and 39-week duration, respectively, findings included vasodilation, increases in serum calcium, decreases in serum phosphorus, and soft tissue mineralization at doses ≥10 mcg/kg/day. The 10 mcg/kg/day dose resulted in systemic exposures to abaloparatide in rats and monkeys that were 2 and 3 times, respectively, the exposure in humans at daily subcutaneous doses of 80 mcg.

Pharmacologic effects of abaloparatide on the skeleton were assessed in 12- and 16-month studies in ovariectomized (OVX) rats and monkeys, at doses up to 11- and 1-times human exposure at the recommended subcutaneous dose of 80 mcg, respectively (based on AUC comparisons). In these animal models of postmenopausal osteoporosis, treatment with abaloparatide resulted in dose-dependent increases in bone mass at vertebral and/or nonvertebral sites, correlating with increases in bone strength. The anabolic effect of abaloparatide was due to the predominant increase in osteoblastic bone formation and was evidenced by increases in trabecular thickness and/or cortical thickness due to endosteal bone apposition. Abaloparatide maintained or improved bone quality at all skeletal sites evaluated and did not cause any mineralization defects.

In an 8-week study in androgen-deficient orchiectomized (ORX) male rats, a male osteoporosis model, the effects of 5 and 25 mcg/kg/day abaloparatide (≥47-fold clinical exposures by AUC) were examined on bone formation, bone mass, and bone strength. Abaloparatide induced bone formation and improved cortical and trabecular BMD, geometry, and architecture without increasing parameters of bone resorption.

14 CLINICAL STUDIES

14.1 Efficacy Study in Women with Postmenopausal Osteoporosis

The efficacy of TYMLOS for the treatment of postmenopausal osteoporosis was evaluated in Study 003 (NCT 01343004), an 18-month, randomized, multicenter, double-blind, placebo-controlled clinical trial in postmenopausal women aged 49 to 86 years (mean age of 69) who were randomized to receive TYMLOS 80 mcg (N = 824) or placebo (N = 821) given subcutaneously once daily. Approximately 80% of patients were Caucasian, 16% were Asian, and 3% were Black; 24% were Hispanic. At baseline, the mean T-scores were -2.9 at the lumbar spine, -2.1 at the femoral neck, and -1.9 at the total hip. At baseline, 24% of patients had at least one prevalent vertebral fracture and 48% had at least one prior nonvertebral fracture. Patients took daily supplemental calcium (500 to 1000 mg) and vitamin D (400 to 800 IU).

The efficacy study was extended as Study 005 (NCT 01657162), an open-label study where patients were no longer receiving TYMLOS or placebo but were maintained in their original randomized treatment group and received 70 mg alendronate weekly, with calcium and vitamin D supplements for 6 months. Study 005 enrolled 1139 patients, representing 92% of patients who completed Study 003. This included 558 patients who had previously received TYMLOS and 581 patients who had previously received placebo. The cumulative 25-month efficacy dataset included 18 months of exposure to TYMLOS or placebo in Study 003, 1 month of no treatment, followed by 6 months of alendronate therapy in Study 005. Study 005 was then continued to complete 18 months of additional alendronate exposure during which time patients were no longer blinded to their original Study 003 treatment group.

Effect on New Vertebral Fractures

The primary endpoint was the incidence of new vertebral fractures in patients treated with TYMLOS compared to placebo. TYMLOS resulted in a significant reduction in the incidence of new vertebral fractures compared to placebo at 18 months (0.6% TYMLOS compared to 4.2% placebo, p <0.0001). The absolute risk reduction in new vertebral fractures was 3.6% at 18 months and the relative risk reduction was 86% for TYMLOS compared to placebo (Table 3). The incidence of new vertebral fractures at 25 months was 0.6% in patients treated with TYMLOS then alendronate, compared to 4.4% in patients treated with placebo then alendronate (p <0.0001). The relative risk reduction in new vertebral fractures at 25 months was 87% for patients treated with TYMLOS then alendronate, compared to patients treated with placebo then alendronate, and the absolute risk reduction was 3.9% (Table 3). After 24 months of open-label alendronate therapy, the vertebral fracture risk reduction achieved with TYMLOS therapy was maintained.

Table 3: Percentage of Postmenopausal Women with Osteoporosis with New Vertebral Fractures (modified Intent to Treat Population) [Includes patients who had both pre- and post-treatment spine radiographs in Study 003] [Includes patients who had both pre- and post-treatment spine radiographs in Study 005]
 | Percentage of Postmenopausal Women With Fractures |  | Absolute Risk Reduction (%) (95% CI [Confidence Interval]) | Relative Risk Reduction (%) (95% CI)
 | TYMLOS (N=690) (%) | Placebo (N=711) (%) | Absolute Risk Reduction (%) (95% CI [Confidence Interval]) | Relative Risk Reduction (%) (95% CI)
0-18 months | 0.6 | 4.2 | 3.6 (2.1, 5.4) | 86 (61, 95)
 | TYMLOS/ Alendronate (N=544) (%) | Placebo/ Alendronate (N=568) (%)
0-25 months | 0.6 | 4.4 | 3.9 (2.1, 5.9) | 87 (59, 96)

Effect on Nonvertebral Fractures

TYMLOS resulted in a significant reduction in the incidence of nonvertebral fractures at the end of the 18 months of treatment plus 1 month follow-up where no drug was administered (2.7% for TYMLOS-treated patients compared to 4.7% for placebo-treated patients). The relative risk reduction in nonvertebral fractures for TYMLOS compared to placebo was 43% (logrank test p = 0.049) and the absolute risk reduction was 2.0%.

Following 6 months of alendronate treatment in Study 005, the cumulative incidence of nonvertebral fractures at 25 months was 2.7% for women in the prior TYMLOS group compared to 5.6% for women in the prior placebo group (Figure 1). At 25 months, the relative risk reduction in nonvertebral fractures was 52% (logrank test p = 0.017) and the absolute risk reduction was 2.9%.

Figure 1: Cumulative Incidence of Nonvertebral Fractures [Excludes fractures of the sternum, patella, toes, fingers, skull and face and those associated with high trauma.] over 25 Months (Intent to Treat Population) [Includes patients randomized in Study 003]

TYMLOS demonstrated consistent reductions in the risk of vertebral and nonvertebral fractures regardless of age, years since menopause, presence or absence of prior fracture (vertebral, nonvertebral), and BMD at baseline.

Effect on Bone Mineral Density (BMD)

Treatment with TYMLOS for 18 months in Study 003 resulted in significant increases in BMD compared to placebo at the lumbar spine, total hip, and femoral neck, each with p<0.0001 (Table 4). Similar findings were seen following 6 months of alendronate treatment in Study 005 (Table 4).

Table 4: Mean Percent Changes in Bone Mineral Density (BMD) From Baseline to Endpoint in Postmenopausal Women with Osteoporosis (Intent to Treat Population)*† ‡
 | TYMLOS (N=824*) (%) | Placebo (N=821*) (%) | Treatment Difference (%) (95% CI§)
18 Months
Lumbar Spine | 9.2 | 0.5 | 8.8 (8.2, 9.3)
Total Hip | 3.4 | -0.1 | 3.5 (3.3, 3.8)
Femoral Neck | 2.9 | -0.4 | 3.3 (3.0, 3.7)
 | TYMLOS/ Alendronate (N=558†) (%) | Placebo/ Alendronate (N=581†) (%)
25 Months
Lumbar Spine | 12.8 | 3.5 | 9.3 (8.6, 10.1)
Total Hip | 5.5 | 1.4 | 4.1 (3.7, 4.5)
Femoral Neck | 4.5 | 0.5 | 4.1 (3.6, 4.6)
* Includes patients randomized in Study 003
† Includes patients enrolled in Study 005
‡ Last-observation-carried-forward
§ Confidence Interval

There was no evidence of differences in the effects of TYMLOS on BMD across subgroups defined by age, years since menopause, race, ethnicity, geographic region, presence or absence of prior fracture (vertebral, nonvertebral), and BMD at baseline.

Effect on Bone Histology

Bone biopsy specimens were obtained from 71 patients with osteoporosis after 12 – 18 months of treatment (36 in the TYMLOS group and 35 in the placebo group). Of the biopsies obtained, 55 were adequate for quantitative histomorphometry assessment (27 in the TYMLOS group and 28 in the placebo group). Qualitative and quantitative histology assessment showed normal bone architecture and no evidence of woven bone, marrow fibrosis, or mineralization defects.

14.2 Men with Osteoporosis

The efficacy of TYMLOS for the treatment of men with osteoporosis was evaluated in Study 019 (NCT 03512262), a 12-month, randomized, multicenter, double-blind, placebo-controlled clinical trial in men aged 42 to 85 years (mean age of 68) who were randomized to receive TYMLOS 80 mcg (N = 149) or placebo (N = 79) given subcutaneously once daily. Approximately 95% of patients were Caucasian, 4% were Asian, and <1% (0.4%) were Black; 16% were Hispanic. At baseline, the mean T-scores were -2.1 at the lumbar spine, -2.1 at the femoral neck, and -1.7 at the total hip. Patients took daily supplemental calcium (500 to 1000 mg) and vitamin D (400 to 800 IU).

Effect on Bone Mineral Density (BMD)

The primary endpoint was the percent change from baseline in lumbar spine BMD at 12 months in patients treated with TYMLOS compared to placebo. Treatment with TYMLOS for 12 months in Study 019 resulted in significant increases in BMD compared to placebo at the lumbar spine, total hip, and femoral neck, each with p<0.0001 (Table 5).

Table 5: Mean Percent Changes in Bone Mineral Density (BMD) From Baseline to 12 Months in Men with Osteoporosis (Intent to Treat Population)
 | TYMLOS (N=149 [Includes patients randomized in Study 019]) (%) | Placebo (N=79) (%) | Treatment Difference (%) (99% CI [Confidence Interval])
12 Months
Lumbar Spine | 8.5 | 1.2 | 7.3 (5.1, 9.6)
Total Hip | 2.1 | <0.1 | 2.1 (1.0, 3.2)
Femoral Neck | 3.0 | 0.2 | 2.8 (1.4, 4.2)

There was no evidence of differences in the effects of TYMLOS on BMD at Month 12 across subgroups defined by age, race, ethnicity, geographic region, presence or absence of prior fracture, and BMD at baseline.

16 HOW SUPPLIED/STORAGE AND HANDLING

16.1 How Supplied

TYMLOS (abaloparatide) injection is a clear and colorless solution, available as a pre-assembled single-patient-use disposable pen (NDC 70539-001-01) packaged in a cardboard carton (NDC 70539-001-02) with the Instructions for Use and Medication Guide. Each disposable pen embodies a glass cartridge that contains 3120 mcg of abaloparatide in 1.56 mL (2000 mcg/mL). Each pen provides a 30-day supply for once daily injection of 80 mcg abaloparatide in 40 mcL.

Sterile needles are not included.

16.2 Storage and Handling

- Before first use, store TYMLOS under refrigeration between 2°C to 8°C (36°F to 46°F).
- After first use, store for up to 30 days at 20°C to 25°C (68°F to 77°F).
- Do not freeze or subject to heat.

17 PATIENT COUNSELING INFORMATION

Advise the patient to read the FDA-approved patient labeling (Medication Guide and Instructions for Use).

Risk of Osteosarcoma

Advise patients that the active ingredient in TYMLOS, abaloparatide, caused a dose-dependent increase in the incidence of osteosarcoma in male and female rats and that it is unknown whether TYMLOS will cause osteosarcoma in humans [see Warnings and Precautions (5.1)].

Instruct patients to promptly report signs and symptoms of possible osteosarcoma such as persistent localized pain or occurrence of a new soft tissue mass that is tender to palpation.

Hypercalcemia

Advise patients that TYMLOS may cause hypercalcemia and discuss the symptoms of hypercalcemia (e.g., nausea, vomiting, constipation, lethargy, muscle weakness) [see Warnings and Precautions (5.3)].

Instruct patients to promptly report signs and symptoms of hypercalcemia.

Orthostatic Hypotension

Advise patients to sit or lie down if they feel lightheaded or have palpitations after the injection until their symptoms resolve. If these symptoms persist or worsen, advise patients to consult their healthcare provider before continuing treatment [see Dosage and Administration (2.2)].

Hypersensitivity Reactions

Advise patients to seek immediate medical attention if they experience signs or symptoms of a hypersensitivity reaction including anaphylaxis, dyspnea, or urticaria [see Contraindications (4) and Adverse Reactions (6.2)].

Use of TYMLOS Pen

Instruct patients and caregivers who administer TYMLOS on how to properly use the TYMLOS pen and to follow sharps disposal recommendations [see Dosage and Administration (2.2)]. Advise patients not to share their TYMLOS pen or needles with other patients and not to transfer the contents of the pen to a syringe.

Advise patients that each TYMLOS pen can be used for up to 30 days, and after the 30-day use period, to discard the TYMLOS pen, even if it still contains unused solution [see How Supplied/Storage and Handling (16.2)].

Manufactured for:
Radius Health, Inc.
22 Boston Wharf Road, 7th Floor
Boston, MA 02210

TYMLOS is a registered trademark of Radius Health, Inc.

Copyright © 2017, Radius Health, Inc. All rights reserved.

US-PI-000001-v11.0

MEDICATION GUIDE
TYMLOS® (tim lows')
(abaloparatide)
injection, for subcutaneous use

What is the most important information I should know about TYMLOS?

TYMLOS may cause serious side effects including:

- Possible bone cancer (osteosarcoma). During animal drug testing, the medicine in TYMLOS caused some rats to develop a bone cancer called osteosarcoma. It is not known if people who take TYMLOS will have a higher chance of getting osteosarcoma.
  - Tell your healthcare provider right away if you have pain in your bones, pain in any areas of your body that does not go away, or any new or unusual lumps or swelling under your skin that is tender to touch.

What is TYMLOS?

TYMLOS is a prescription medicine used to:

- treat osteoporosis in postmenopausal women who are at high risk for bone fracture, or who cannot use another osteoporosis treatment or other osteoporosis treatments did not work well. TYMLOS can decrease the chance of having a fracture of the spine and other bones in postmenopausal women with thinning and weakening bones (osteoporosis)
- increase bone density in men with osteoporosis who are at high risk for bone fracture, or who cannot use another osteoporosis treatment or other osteoporosis treatments did not work well

It is not known if TYMLOS is safe and effective for children 18 years and younger. TYMLOS should not be used in children and young adults whose bones are still growing.
It is not recommended that people use TYMLOS for more than 2 years during their lifetime.

Do not take TYMLOS:

- if you had an allergic reaction to abaloparatide, or any of the other ingredients in TYMLOS. See the end of this Medication Guide for a complete list of ingredients in TYMLOS.

Before you take TYMLOS, tell your healthcare provider about all of your medical conditions, including if you:

- have Paget's disease of the bone or other bone disease.
- have or have had cancer in your bones.
- have or have had radiation therapy involving your bones.
- have or have had too much calcium in your blood.
- have or have had an increase in your parathyroid hormone (hyperparathyroidism).
- will have trouble injecting yourself with the TYMLOS pen and do not have someone who can help you.
- are pregnant or plan to become pregnant. TYMLOS is not for pregnant women.
- are breastfeeding or plan to breastfeed. It is not known if TYMLOS passes into your breast milk. You and your healthcare provider should decide if you will take TYMLOS or breastfeed. You should not do both.

Tell your healthcare provider about all the medicines you take, including prescription and over-the-counter medicines, vitamins, and herbal supplements.
Know the medicines you take. Keep a list of them to show your healthcare provider or pharmacist each time you get a new medicine.

How should I use TYMLOS?

- Read the detailed Instructions for Use provided with your medicine.
- Use TYMLOS exactly as your healthcare provider tells you to use it.
- Do not try to inject TYMLOS yourself until you or your caregiver receive training from a healthcare provider on the right way to use the TYMLOS pen.
- You should receive your first several injections of TYMLOS where you can sit or lie down, if necessary, until you know how it affects you.
- Inject TYMLOS 1 time each day into your lower stomach area (abdomen) just under your skin (subcutaneous). Avoid giving your injection within the 2-inch area around your belly button (navel).
- Talk to your healthcare provider about how to change (rotate) your injection site for each injection. Do not give TYMLOS in your veins (intravenously) or deep into your muscles (intramuscularly).
- You can take TYMLOS with or without food or drink.
- Take TYMLOS at about the same time each day.
- If you forget or cannot take TYMLOS at your usual time, take it as soon as you can on that day.
- The TYMLOS pen has enough medicine for 30 days. It is set to give 1 dose of medicine with each injection. Do not take more than 1 injection in the same day.
- Do not transfer the medicine from the TYMLOS pen to a syringe. This can cause you to use the wrong dose of TYMLOS. If you do not have pen needles to use with your TYMLOS pen, talk with your healthcare provider.
- Do not share your TYMLOS pen or pen needles with other people, even if the needle has been changed. You may give other people a serious infection or get a serious infection from them.
- TYMLOS should look clear and colorless. Do not use TYMLOS if it has particles in it, or if it is cloudy or colored.
- Your healthcare provider may do blood and urine tests during your treatment with TYMLOS.
- Your healthcare provider may ask you to have a bone mineral density test after your treatment with TYMLOS.
- If you take more TYMLOS than prescribed you may have symptoms such as muscle weakness, low energy, headache, nausea, dizziness (especially when getting up after sitting for a while), and a faster heartbeat. Stop taking TYMLOS and call your healthcare provider right away.
- You should not use TYMLOS for more than 2 years over your lifetime.
- If your healthcare provider recommends calcium and vitamin D supplements, you can take them while using TYMLOS.

What are the possible side effects of TYMLOS?

TYMLOS may cause serious side effects including:

- See "What is the most important information I should know about TYMLOS?"
- Decrease in blood pressure when you change positions. Some people may feel dizzy, have a faster heartbeat, or feel lightheaded soon after the TYMLOS injection is given. These symptoms generally go away within a few hours. Take your injections of TYMLOS in a place where you can sit or lie down right away if you get these symptoms. If your symptoms get worse or do not go away, stop taking TYMLOS and call your healthcare provider.
- Increased blood calcium (hypercalcemia). TYMLOS can cause some people to have a higher blood calcium level than normal. Your healthcare provider may check your blood calcium before you start and during your treatment with TYMLOS. Tell your healthcare provider if you have nausea, vomiting, constipation, low energy, or muscle weakness. These may be signs there is too much calcium in your blood.
- Increased urine calcium (hypercalciuria). TYMLOS can cause some people to have higher levels of calcium in their urine than normal. Increased calcium may also cause you to develop kidney stones (urolithiasis) in your kidneys, bladder, or urinary tract. Tell your healthcare provider right away if you get any symptoms of kidney stones which may include pain in your lower back or lower stomach area, pain when you urinate, or blood in your urine.

The most common side effects of TYMLOS in women with postmenopausal osteoporosis include:

- dizziness

- fast heartbeat

- upper stomach pain

- nausea

- feeling tired (fatigue)

- spinning feeling (vertigo)

- headache

The most common side effects of TYMLOS in men with osteoporosis include:

- redness at injection site

- pain at injection site

- nausea

- dizziness

- bruising

- abdominal pain

- joint pain

- abdominal bloating

- bone pain

- swelling at injection site

- diarrhea

These are not all the possible side effects of TYMLOS. Call your doctor for medical advice about side effects. You may report side effects to FDA at 1-800-FDA-1088.

How should I store TYMLOS?

- Before first use, store TYMLOS pens in the refrigerator between 36°F to 46°F (2°C to 8°C).
- After first use, store your TYMLOS pen for up to 30 days at room temperature between 68°F to 77°F (20°C to 25°C).
- Do not freeze the TYMLOS pen or expose it to heat.
- Do not use TYMLOS after the expiration date printed on the pen and packaging.
- Throw away the TYMLOS pen after 30 days even if some medicine is left in the pen (see "Instructions for Use").

Keep TYMLOS and all medicines out of the reach of children.

General information about the safe and effective use of TYMLOS.
Medicines are sometimes prescribed for purposes other than those listed in a Medication Guide. Do not use TYMLOS for a condition for which it was not prescribed. Do not give TYMLOS to other people, even if they have the same condition you have. It may harm them.
You can ask your pharmacist or healthcare provider for information about TYMLOS that is written for health professionals.

What are the ingredients in TYMLOS?
Active ingredient: abaloparatide
Inactive ingredients: acetic acid, phenol, sodium acetate trihydrate, and water for injection.

Radius Health, Inc., 22 Boston Wharf Road, 7th Floor, Boston, MA 02210

TYMLOS is a registered trademark of Radius Health, Inc. US-MG-000001 v8.0

Copyright © 2023, Radius Health, Inc. All rights reserved.

For more information about TYMLOS, visit our website at www.TYMLOS.com or call Radius Health, Inc., at 1-855-672-3487.

This Medication Guide has been approved by the U.S. Food and Drug Administration.

Revised: 12/2023

INSTRUCTIONS FOR USE
TYMLOS® (tim lows')
(abaloparatide)
injection, for subcutaneous use

Instructions for Use
Read and follow this Instructions for Use so that you inject TYMLOS pen the right way. Call your healthcare provider if you have any questions about the right way to inject the TYMLOS pen.

Important information about your TYMLOS pen

- Do not try to inject TYMLOS yourself until you or your caregiver receive training from a healthcare provider on the right way to use TYMLOS pen.
- Do not share your TYMLOS pen or pen needles with other people, even if the needle has been changed. You may give other people a serious infection, or get a serious infection from them.
- Each TYMLOS pen is a prefilled pen containing 30 doses of TYMLOS. Each dose will contain 80 mcg of TYMLOS. You do not have to measure your dose. The pen measures each dose of TYMLOS for you.
- Use a new pen needle for each injection. Keep the cap on the TYMLOS pen when not using the pen.
- Before using the pen always check the label to be sure it is your TYMLOS pen.
- Do not use your TYMLOS pen if it looks damaged. If you drop your TYMLOS pen or it becomes damaged, call your healthcare provider or pharmacist or call 1-855-672-3487.
- To clean your TYMLOS pen, wipe the outside of the pen with a clean, damp cloth, if needed.
- The TYMLOS pen is not recommended for use by the blind or visually impaired without the help of a person trained in the right way to use the pen.

Pen needles to use with your TYMLOS pen

- Pen needles are not included with your TYMLOS pen. You will need a prescription from your healthcare provider to get pen needles from your pharmacy.
- The correct needles to use with your TYMLOS pen are 5 to 8 mm, 31-gauge needles. Compatible needles include Clickfine®, BD Ultra-Fine™, MedtFine®, Easy Comfort, Clever Choice™ Comfort EZ™, and SureComfort™. If you are not sure what type of needle to use, ask your healthcare provider or pharmacist.

Supplies you will need for each injection using your TYMLOS pen

- 1 TYMLOS pen
- 1 pen needle
- 1 alcohol swab
- 1 cotton ball or gauze pad
- 1 sharps disposal container for pen needles and TYMLOS pens. See "How should I throw away (dispose) of the pen needles and TYMLOS pens?" in the far right column.

How should I store the TYMLOS pen?

- Before first use, store TYMLOS pens in the refrigerator between 36°F to 46°F (2°C to 8°C).
- Do not store pens with the needle attached.
- Do not freeze the TYMLOS pen or expose it to heat.

During 30 days of use:

- After first use, store the TYMLOS pen for up to 30 days at room temperature between 68°F to 77°F (20°C to 25°C).
- Keep the pen cap on your TYMLOS pen when storing. Do not store the TYMLOS pen with needle attached.
- Use your TYMLOS pen for only 30 days.
- Write down the date of your first use of TYMLOS here: _____/_____/_____. Throw away your TYMLOS pen 30 days after first opening it even if it still contains unused medicine.

Keep the TYMLOS pen, pen needles and all medicines out of the reach of children.

How should I throw away (dispose) of the pen needles and TYMLOS pens?

- Throw away (dispose of) your TYMLOS pen, in a FDA-cleared sharps disposal container or puncture resistant container, 30 days after first opening it even if it still contains unused medicine.
- Put your used pen needles in a FDA-cleared sharps disposal container right away after use. Do not throw away (dispose of) your used sharps disposal container in your household trash.
- If you do not have a FDA-cleared sharps disposal container, you may use a household container that is:
  - made of a heavy-duty plastic,
  - can be closed with a tight-fitting, puncture-resistant lid, without sharps being able to come out,
  - upright and stable during use,
  - leak-resistant, and properly labeled to warn of hazardous waste inside the container.
- When your sharps disposal container is almost full, you will need to follow your community guidelines for the right way to dispose of your sharps disposal container. There may be state or local laws about how you should throw away used needles, syringes, and prefilled syringes.
- For more information about safe sharps disposal, and for specific information about sharps disposal in the state that you live in, go to FDA's website at: https://www.fda.gov/safesharpsdisposal.
- Do not dispose of your used sharps disposal container in your household trash unless your community guidelines permit this. Do not recycle your used sharps disposal container.

For more information about the TYMLOS pen

For more information, go to www.TYMLOS.com or call 1-855-672-3487.

Manufactured for:

Radius

Radius Health, Inc.
22 Boston Wharf Road, 7th Floor
Boston, MA 02210

TYMLOS is a registered trademark of Radius Health, Inc.
US-IFU-000001-v8.0

Begin the injection.

Check the TYMLOS® pen

Step 1. Wash and dry your hands.

Step 2. Check the expiration date (Exp.) on the TYMLOS pen.

- Do not use the pen if the expiration date has passed.
- Call your healthcare provider or pharmacist if the expiration date has passed.

Attach pen needle to your TYMLOS pen

Step 3. Pull off the pen cap from your TYMLOS pen. (See Figure D.)

- Check the TYMLOS cartridge. The liquid should be clear, colorless, and free of particles; if not, do not use.

Step 4. Pull off the protective paper from the outer needle cap of your pen needle. (See Figure E.)

Step 5. Keep the needle straight and screw it onto the pen until fixed; a secure fit is ensured even if there is no noticeable stop. Do not over-tighten. (See Figure F.)

Step 6. Pull off the outer pen needle cap from the pen needle and keep it to use after your injection. (See Figure G.)

Step 7. Carefully pull off the inner pen needle cap and dispose of it. (See Figure H.)

Step 8. If you are using this pen for the first time, go to the "New pen setup - Day 1 Only" section to prime your pen.

- If you have already used this pen before, go to Step 13 for Days 2 through 30.

New pen setup – Day 1 Only (Priming your TYMLOS pen)

Do not repeat new pen setup on Days 2 through 30.

Step 9. The "New pen setup" removes air bubbles (primes your pen). You only need to prime your pen on Day 1 for each new pen. Otherwise, you will waste medicine.

- Skip Steps 10 through 12 on Days 2 through 30.

Step 10. Turn the dose knob on your TYMLOS pen away from you (clockwise) until it stops. (See Figure I.)

Note: You will see " • 80 " lined up in the dose display window.

Step 11. Hold the TYMLOS pen with the pen needle pointing up. Tap lightly with your finger on the cartridge holder to move any air bubbles in the cartridge to the top of the cartridge. (See Figure J.)

Note: Do Step 11 even if you do not see air bubbles.

Step 12. Press the green injection button until it will not go any further. (See Figure K).

Note: You should see liquid come out of the needle tip.

Note: You will see "•0" lined up in the dose display window.

What should I do if liquid does not come out of the needle tip?

- If you do not see a drop of TYMLOS, repeat Steps 10 through 12. A drop of liquid should come out of the needle tip.
- If you still do not see a drop of liquid call your healthcare provider or pharmacist and use a new TYMLOS pen.
- When you are ready to use your new TYMLOS pen for the first time, remember to repeat all Steps 9 through 12 to prime your new TYMLOS pen.

Set the dose on your TYMLOS pen

Do not push the green injection button while setting your dose.

Step 13. Turn the dose knob on your pen away from you (clockwise) until the dose knob stops and "•80" is lined up in the dose display window. (See Figure L.)

If you set the dose before you are ready to give your injection, turn the dose knob toward you (counter-clockwise) until "•0" is in the dose display window.

If you are not able to set the TYMLOS pen to "•80", dispose of the pen and use a new TYMLOS pen for your injection, repeating Steps 1 through 13.

- If the pen cannot be set to "•80", there is not enough medicine in the TYMLOS pen for your full dose. See "How should I throw away (dispose) of the pen needles and TYMLOS pens?" on the other side.

Choose and clean your injection site

Step 14. Injections should be given in the lower stomach area (abdomen). (See Figure M.) Avoid the 2-inch area around your belly button (navel).

For each injection, change (rotate) your injection site around your abdomen. Talk to your healthcare provider about how to change (rotate) your injection site for each injection. Do not use the same injection area for each injection. Do not inject into areas where the skin is tender, bruised, red, scaly, or hard. Avoid areas with scars or stretch marks.

Step 15. Wipe the injection site with an alcohol swab and allow it to dry. Do not touch, fan, or blow on the injection site after you have cleaned it.

Giving your TYMLOS pen injection

Read Step 16 and Step 17 before you give your injection.

Inject your TYMLOS pen the way your healthcare provider has shown you.

Step 16. (See Figure N.)

- Hold the pen so you can see the dose display window during the injection.
- Insert the pen needle straight into your skin.

Step 17. (See Figure O.)

- Press the green injection button until it cannot go any further and "•0" is in the dose display window. Do not move the TYMLOS pen after inserting the needle.
- Continue to press the green injection button while counting to 10. Counting to 10 will allow the full dose of TYMLOS to be given.

Step 18. After counting to 10, release your finger from the green injection button and slowly remove the TYMLOS pen from the injection site by pulling the pen needle straight out.

Remove the pen needle

Step 19. Carefully place the outer needle cap back on the pen needle. Press on the outer needle cap until it snaps into place and is secure. (See Figure P.)

Caution: To prevent needle stick injury, carefully follow Step 20.

Step 20. Unscrew the capped needle (like unscrewing a cap from a bottle). To unscrew the capped needle you may need to turn it 8 or more turns and then gently pull until the capped needle comes off. (See Figure Q.)

Note: Do not push on the outer needle cap while unscrewing the needle. You should see a gap widening between the outer needle cap and the pen as you unscrew the needle. (See Figure R.)

Replace pen cap

Step 21. Firmly replace the pen cap onto the TYMLOS pen. (See Figure S.)
Keep the pen cap on your TYMLOS pen between injections.

After your injection

Step 22. Press a cotton ball or gauze pad over the injection site and hold for 10 seconds. Do not rub the injection site. You may have slight bleeding. This is normal.
You may cover the injection site with a small adhesive bandage, if needed.

- Dispose of the pen needle. See "How should I throw away (dispose) of the pen needles and TYMLOS pens?" .

This Instructions for Use has been approved by the U.S. Food and Drug Administration.

Issued:04/2021

PRINCIPAL DISPLAY PANEL - 80 mcg Prefilled Pen Label

NDC 70539-001-01
Rx only

Read Instructions for Use BEFORE injecting.

Date of first use ________/________/________.
Discard unused portion 30 days after first opening.

TYMLOS®
(abaloparatide) injection

80 mcg per dose
3120 mcg/1.56 mL (2000 mcg/mL)

For subcutaneous use
For Single Patient Use Only
Each prefilled pen will deliver 30 subcutaneous doses.
Before first use, keep in refrigerator at 2°C – 8°C (36°F – 46°F).
After first use, store for up to 30 days at 20°C – 25°C
(68°F – 77°F). Do not freeze or subject to heat.
Mfg. for: Radius Health, Inc.
Boston, MA 02210 USA
10006074-04

Lot:
Exp.:

PRINCIPAL DISPLAY PANEL - 80 mcg Prefilled Pen Box

NDC 70539-001-02

TYMLOS®
(abaloparatide) injection

80 mcg per dose
3120 mcg/1.56 mL (2000 mcg/mL)

For subcutaneous use
For Single Patient Use Only

Rx only
Sterile

1 prefilled pen
Needles not included

Each prefilled pen will deliver
30 subcutaneous doses.

Dispense the enclosed
Medication Guide
and Instructions for Use
to each patient.

PRINCIPAL DISPLAY PANEL - Sample 80 mcg Prefilled Pen Label

NDC 70539-001-99
Rx only

Read Instructions for Use BEFORE injecting.

Date of first use ________/________/________.
Discard unused portion 30 days after first opening.

TYMLOS®
(abaloparatide) injection

SAMPLE—NOT FOR SALE

80 mcg per dose
3120 mcg/1.56 mL (2000 mcg/mL)

For subcutaneous use
For Single Patient Use Only
Each prefilled pen will deliver 30 subcutaneous doses.
Before first use, keep in refrigerator at 2°C – 8°C (36°F – 46°F).
After first use, store for up to 30 days at 20°C – 25°C
(68°F – 77°F). Do not freeze or subject to heat.
Mfg. for: Radius Health, Inc.
Boston, MA 02210 USA
10006645-04

Lot:
Exp.:

PRINCIPAL DISPLAY PANEL - 80 mcg Prefilled Pen Box - Sample

NDC 70539-001-98

TYMLOS®
(abaloparatide) injection

80 mcg per dose
3120 mcg/1.56 mL (2000 mcg/mL)

For subcutaneous use
For Single Patient Use Only

Sterile

Rx only
SAMPLE—NOT FOR SALE

1 prefilled pen
Needles not included

Each prefilled pen will deliver
30 subcutaneous doses.

Dispense the enclosed
Medication Guide
and Instructions for Use
to each patient.